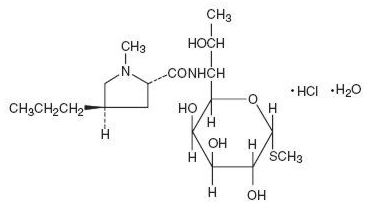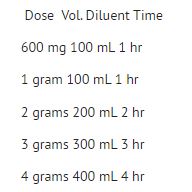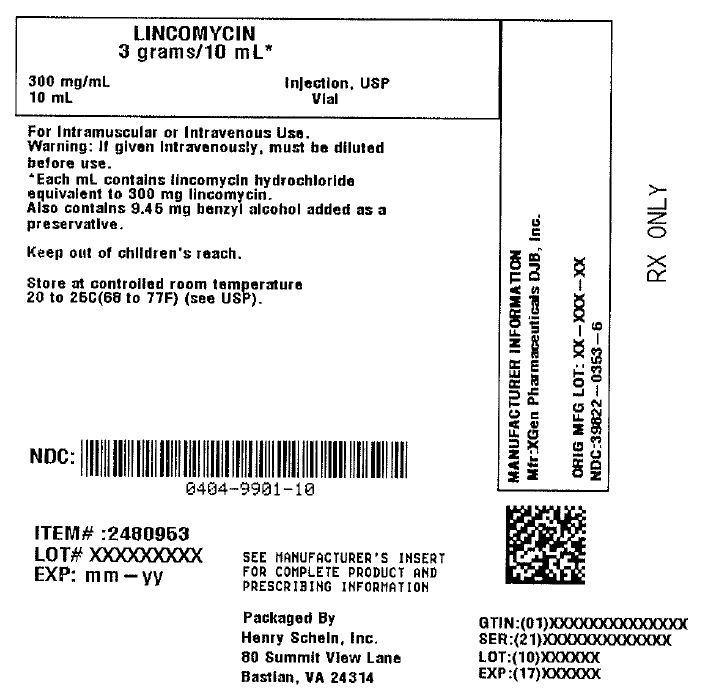 DRUG LABEL: LINCOMYCIN
NDC: 0404-9901 | Form: INJECTION, SOLUTION
Manufacturer: Henry Schein, Inc.
Category: prescription | Type: HUMAN PRESCRIPTION DRUG LABEL
Date: 20251031

ACTIVE INGREDIENTS: LINCOMYCIN HYDROCHLORIDE 300 mg/1 mL
INACTIVE INGREDIENTS: BENZYL ALCOHOL 9.45 mg/1 mL

Lincomycin

SPL UNCLASSIFIED SECTION

To reduce the development of drug-resistant bacteria and maintain the effectiveness of Lincomycin and other antibacterial drugs, Lincomycin should be used only to treat or prevent infections that are proven or strongly suspected to be caused by bacteria.

BOXED WARNINIG

WARNING

Clostridium difficile associated diarrhea (CDAD) has been reported with use of nearly all antibacterial agents, including Lincomycin and may range in severity from mild diarrhea to fatal colitis. Treatment with antibacterial agents alters the normal flora of the colon leading to overgrowth of C. difficile.

Because lincomycin therapy has been associated with severe colitis which may end fatally, it should be reserved for serious infections where less toxic antimicrobial agents are inappropriate, as described in the INDICATIONS AND USAGE section. It should not be used in patients with nonbacterial infections such as most upper respiratory tract infections.

C.diffficile produces toxins A and B which contribute to the development of CDAD. Hypertoxin producing strains of C. difficile cause increased morbidity and mortality, as these infections can be refractory to antimicrobial therapy and may require colectomy. CDAD must be considered in all patients who present with diarrhea following antibacterial use. Careful medical history is necessary since CDAD has been reported to occur over two months after the administration of antibacterial agents.

If CDAD is suspected or confirmed, ongoing antibacterial use not directed against C. difficile may need to be discontinued. Appropriate fluid and electrolyte management, protein supplementation, antibacterial treatment of C. difficile, and surgical evaluation should be instituted as clinically indicated.

DESCRIPTION

Lincomycin Injection is a sterile solution which contains lincomycin hydrochloride which is the monohydrated salt of lincomycin, a substance produced by the growth of a member of the lincolnensis group of Streptomyces lincolnensis (Fam. Streptomycetaceae). The chemical name for lincomycin hydrochloride is Methyl 6,8-dideoxy-6-(1-methyl-trans-4-propyl-L-2-pyrolidinecarboxamido)-1-thio-D-erythro-α-D-galacto-octopyranoside monohydrochloride monohydrate. The molecular formula of lincomycin hydrochloride is C18H34N2O6S.HCl.H2O and the molecular weight is 461.01.

The structural formula is represented below:

Lincomycin hydrochloride is a white or practically white, crystalline powder and is odorless or has a faint odor. Its solutions are acid and are dextrorotatory. Lincomycin hydrochloride is freely soluble in water; soluble in dimethylformamide and very slightly soluble in acetone.

CLINICAL PHARMAcOLOGY

Intramuscular administration of a single dose of 600 mg of lincomycin produces average peak serum concentrations of 11.6 µg/mL at 60 minutes and maintains therapeutic concentrations for 17 to 20 hours for most susceptible gram-positive organisms. Urinary excretion after this dose ranges from 1.8 to 24.8 percent (mean: 17.3 percent).

A two hour intravenous infusion of 600 mg of lincomycin achieves average peak serum concentrations of 15.9 µg/mL and yields therapeutic concentrations for 14 hours for most susceptible gram-positive organisms. Urinary excretion ranges from 4.9 to 30.3 percent (mean: 13.8 percent).

The biological half-life after intramuscular or intravenous administration is 5.4 ± 1.0 hours. The serum half-life of lincomycin may be prolonged in patients with severe impairment of renal function compared to patients with normal renal function. In patients with abnormal hepatic function, serum half-life may be twofold longer than in patients with normal hepatic function. Hemodialysis and peritoneal dialysis are not effective in removing lincomycin from the serum.

Tissue level concentrations indicate that bile is an important route of excretion. Significant concentrations have been demonstrated in the majority of body tissues. Although lincomycin appears to diffuse into cerebrospinal fluid (CSF), concentrations of lincomycin in the CSF appear inadequate for the treatment of meningitis.

Microbiology:

Lincomycin has been shown to be active against most strains of the following organisms both in vitro and in clinical infections: (see INDICATIONS AND USAGE).
Staphylococcus aureus
Streptococcus pneumoniae

The following in vitro data are available; but their clinical significance is unknown.

Lincomycin has been shown to be active in vitro against the following microorganisms; however, the safety and efficacy of Lincomycin in treating clinical infections due to these organisms have not been established in adequate and well controlled trials.

Gram-positive bacteria::
Corynebacterium diphtheriae
Streptococcus pyogenes
Viridans group streptococci

Anaerobic bacteria:
Clostridium tetani
Clostridium perfringens

Cross resistance has been demonstrated between clindamycin and lincomycin. Resistance is most often due to methylation of specific nucleotides in the 23S RNA of the 50S ribosomal subunit, which can determine cross resistance to macrolides and streptogramins B (MLS phenotype). Macrolide-resistant isolates of these organisms should be tested for inducible resistance to lincomycin/clindamycin using the D-zone test or other appropriate method.

There are currently no antimicrobial susceptibility testing (AST) interpretive criteria for Lincomycin.

CONTRAINDICATIONS

This drug is contraindicated in patients previously found to be hypersensitive to lincomycin or clindamycin.

WARNINGS

See WARNING Box.

Clostridium difficile associated diarrhea

Clostridium difficile associated diarrhea (CDAD) has been reported with use of nearly all antibacterial agents, including Lincomycin, and may range in severity from mild diarrhea to fatal colitis. Treatment with antibacterial agents alters the normal flora of the colon leading to overgrowth of C. difficile.

C. difficile produces toxins A and B which contribute to the development of CDAD. Hypertoxin producing strains of C. difficile cause increased morbidity and mortality, as these infections can be refractory to antimicrobial therapy and may require colectomy. CDAD must be considered in all patients who present with diarrhea following antibacterial use. Careful medical history is necessary since CDAD has been reported to occur over two months after the administration of antibacterial agents.

If CDAD is suspected or confirmed, ongoing antibacterial use not directed against C. difficile may need to be discontinued. Appropriate fluid and electrolyte management, protein supplementation, antibacterial treatment of C. difficile, and surgical evaluation should be instituted as clinically indicated.

Hypersensitivity
Serious hypersensitivity reactions, including anaphylaxis and erythema multiforme, have been reported with use of Lincomycin Injection. If an allergic reaction to Lincomycin occurs, discontinue the drug. (See ADVERSE REACTIONS)

Benzyl Alcohol Toxicity in Pediatric Patients ("Gasping Syndrome")
Lincomycin Injection Sterile Solution contains benzyl alcohol as a preservative. The preservative benzyl alcohol has been associated with serious adverse events, including the "gasping syndrome", and death in pediatric patients. Although normal therapeutic doses of this product ordinarily deliver amounts of benzyl alcohol that are substantially lower than those reported in association with the "gasping syndrome", the minimum amount of benzyl alcohol at which toxicity may occur is not known. The risk of benzyl alcohol toxicity depends on the quantity administered and the liver and kidney's capacity to detoxify the chemical. Premature and low-birth weight infants may be more likely to develop toxicity.

Use in Meningitis — Although lincomycin appears to diffuse into cerebrospinal fluid, levels of lincomycin in the CSF may be inadequate for the treatment of meningitis.

PRECAUTIONS

General
Review of experience to date suggests that a subgroup of older patients with associated severe illness may tolerate diarrhea less well. When Lincomycin is indicated in these patients, they should be carefully monitored for change in bowel frequency.

Lincomycin should be prescribed with caution in individuals with a history of gastrointestinal disease, particularly colitis.

Lincomycin should be used with caution in patients with a history of asthma or significant allergies.

Certain infections may require incision and drainage or other indicated surgical procedures in addition to antibacterial therapy.

The use of Lincomycin may result in overgrowth of nonsusceptible organisms— particularly yeasts. Should superinfections occur, appropriate measures should be taken as indicated by the clinical situation. When patients with pre-existing monilial infections require therapy with Lincomycin, concomitant antimonilial treatment should be given.

The serum half-life of lincomycin may be prolonged in patients with severe impairment of renal function compared to patients with normal renal function. In patients with abnormal hepatic function, serum half-life may be twofold longer than in patients with normal hepatic function.

Patients with severe impairment of renal function and/or abnormal hepatic function should be dosed with caution and serum lincomycin levels monitored during high-dose therapy. (See DOSAGE AND ADMINISTRATION Section.)

Lincomycin should not be injected intravenously undiluted as a bolus, but should be infused over at least 60 minutes as directed in the DOSAGE AND ADMINISTRATION Section.

Prescribing Lincomycin in the absence of a proven or strongly suspected bacterial infection or a prophylactic indication is unlikely to provide benefit to the patient and increases the risk of the development of drug-resistant bacteria.

Information for Patients
Patients should be counseled that antibacterial drugs including Lincomycin should only be used to treat bacterial infections. They do not treat viral infections (e.g., the common cold). When Lincomycin is prescribed to treat a bacterial infection, patients should be told that although it is common to feel better early in the course of therapy, the medication should be taken exactly as directed. Skipping doses or not completing the full course of therapy may (1) decrease the effectiveness of the immediate treatment and (2) increase the likelihood that bacteria will develop resistance and will not be treatable by Lincomycin or other antibacterial drugs in the future.

Diarrhea is a common problem caused by antibacterial which usually ends when the antibacterial is discontinued. Sometimes after starting treatment with antibacterial, patients can develop watery and bloody stools (with or without stomach cramps and fever) even as late as two or more months after having taken the last dose of the antibacterial. If this occurs, patients should contact their physician as soon as possible

Laboratory Tests
During prolonged therapy with Lincomycin, periodic liver and kidney function tests and blood counts should be performed.

Drug Interactions
Lincomycin has been shown to have neuromuscular blocking properties that may enhance the action of other neuro-muscular blocking
agents. Therefore, it should be used in caution in patients receiving such agents.

Antagonism between lincomycin and erythromycin in vitro has been demonstrated. Because of the possible clinical significance, the two drugs should not be administered concurrently.

Carcinogenesis, Mutagenesis, Impairment of Fertility:
The carcinogenic potential of lincomycin has not been evaluated.

Lincomycin was not found to be mutagenic in the Ames Salmonella reversion assay or the V79 Chinese hamster lung cells at the HGPRT locus. It did not induce DNA strand breaks in V79 Chinese hamster lung cells as measured by alkaline elution or chromosomal abnormalities in cultured human lymphocytes. In vivo, lincomycin was negative in both the rat and mouse micronucleus assays and it did not induce sex-linked recessive lethal mutations in the offspring of male Drosophila. However, lincomycin did cause unscheduled DNA syntheses in freshly isolated rat hepatocytes.

Impairment of fertility was not observed in male or female rats given oral 300 mg/kg doses of lincomycin (0.36 times the highest recommended human dose based on mg/m2).

Pregnancy: Pregnancy Category C
Lincomycin Sterile Solution contains benzyl alcohol as a preservative. Benzyl alcohol can cross the placenta.

See WARNINGS.

Teratogenic Effects:

There are no studies on the teratogenic potential of lincomycin in animals or adequate and well-controlled studies of pregnant women.

Nonteratogenic Effects:

Reproduction studies have been performed in rats using oral doses of lincomycin up to 1000 mg/kg (1.2 times the maximum daily human dose based on mg/m²) and have revealed no adverse effects on survival of offspring from birth to weaning.

Nursing Mothers
Lincomycin has been reported to appear in human milk in concentrations of 0.5 to 2.4 mcg/mL. Because of the potential for serious adverse reactions in nursing infants from Lincomycin Injection, a decision should be made whether to discontinue nursing, or to discontinue the drug, taking into account the importance of the drug to the mother.

Pediatric Use
Lincomycin Injection, USP contains benzyl alcohol as a preservative. Benzyl alcohol has been associated with a fatal "Gasping Syndrome" in premature infants. See WARNINGS. Safety and effectiveness in pediatric patients below the age of one month have not been established. (See DOSAGE AND ADMINISTRATION Section.)

ADVERSE REACTIONS

The following reactions have been reported with the use of lincomycin and are listed by System Organ Class. Frequencies are defined as: commom (≥1% and<10%) uncommon (≥0.1% and <1%), rare (≥0.01% and <0.1%) and not known (cannot be estimated from the available data).

Gastrointestinal disorders

Common: persistent diarrhea (4.3%), nausea (1.8%), vomiting (1.6%)

Rare: stomatitis (0.04%)

Not known: glossitis, abdominal discomfort, and pruritus

Skin and subcutaneous tissue disorders

Uncommon: rash (0.8%), urticaria (0.1%)

Rare: pruritus (0.4%)

Infections and infestations

Uncommon: vaginal infection (0.12%)

Not known: pseudomembranous colitis, Clostridium difficile colitis (see WARNINGS)

Blood and lymphatic system disorders

Not known: pancytopenia, agranulocytosis, aplastic anemia, leukopenia, neutropenia, thrombocytopenic purpura

Immune system disorders

Not known: anaphylactic reaction (see WARNINGS) angioedema, serum sickness

Hepatobiliary disorders

Not known: jaundice, liver function test abnormal, transaminases increased

Renal and urinary disorders

Not known: renal impairment, oliguria, proteinuria, azotemia

¹No direct relationship of LINCOCIN to renal damage has been established.

Cardiac disorders

Not known: cardio-respiratory arrest (see DOSAGE AND ADMINISTRATION)

Vascular disorders

Not known: hypotension (see DOSAGE AND ADMINISTRATION), thrombophlebitis²

²Event has been reported with intravenous injection.

Ear and labyrinth disorders

Not known: vertigo, tinnitus
Not known: injection site abscess sterile³, injection site induration³, injection site pain³, injection site irritation³

³Reported with intramuscular injection.

OVERDOSAGE

Serum levels of lincomycin are not appreciably affected by hemodialysis and peritoneal dialysis.

DOSAGE AND ADMINISRATION

If significant diarrhea occurs during therapy, this antibacterial should be discontinued. (See WARNING box.)

INTRAMUSCULAR-Adults: Serious infections—600 mg (2 mL) intramuscularly every 24 hours. More severe infections—600 mg (2 mL) intramuscularly every 12 hours or more often. Pediatric patients over 1 month of age: Serious infections—one intramuscular injection of 10 mg/kg (5 mg/lb) every 24 hours. More severe infections—one intramuscular injection of 10 mg/kg (5 mg/lb) every 12 hours or more often.

INTRAVENOUS Adults:

The intravenous dose will be determined by the severity of the infection. For serious infections doses of 600 mg of lincomycin (2 mL of Lincomycin Injection) to 1 gram are given every 8 to 12 hours. For more severe infections these doses may have to be increased. In life-threatening situations, daily intravenous doses of as much as 8 grams have been given. Intravenous doses are given on the basis of 1 gram of lincomycin diluted in not less than 100 mL of appropriate solution (see PHYSICAL COMPATIBILITIES) and infused over a period of not less than one hour.

These doses may be repeated as often as required to the limit of the maximum recommended daily dose of 8 grams of lincomycin.

Pediatric patients over 1 month of age: 10 to 20 mg/kg/day (5 to 10 mg/lb/day) depending on the severity of the infection may be infused in divided doses as described above for adults.

NOTE: Severe cardiopulmonary reactions have occurred when this drug has been given at greater than the recommended concentration and rate.
SUBCONJUNCTIVAL INJECTION-0.25 mL (75 mg) injected subconjunctivally will result in ocular fluid levels of antibacterial (lasting for at least 5 hours) with MICs sufficient for most susceptible pathogens.

Patients with diminished renal function: When therapy with Lincomycin is required in individuals with severe impairment of renal function, an appropriate dose is 25 to 30% of that recommended for patients with normally functioning kidneys.

HOW SUPPLIED

Lincomycin Injection, USP is available in the following strength and package sizes:

300 mg/mL

2 mL Vials NDC 39822-0350-1 Packaged as 10 vials per carton NDC 39822-0350-2

10 mL Vials NDC 39822-0353-5 Packaged as 10 vials per carton NDC 39822-0353-6

Each mL of Lincomycin Injection, USP contains lincomycin hydrochloride equivalent to lincomycin 300 mg; also benzyl alcohol, 9.45 mg added as preservative.

Store at controlled room temperature 20° to 25°C (68° to 77°F) [see USP]

Product repackaged by: Henry Schein, Inc., Bastian, VA 24314
From Original Manufacturer/Distributor's NDC and Unit of Sale | To Henry Schein Repackaged Product NDC and Unit of Sale | Total Strength/Total Volume (Concentration) per unit
NDC 39822-0353-6 10 Pack | NDC 0404-9901-10 1 10 mL Vial in a bag (Vial bears NDC 39822-0353-5) | 300 mg/mL

ANIMAL PHARMACOLOGY

In vivo experimental animal studies demonstrated the effectiveness of LINCOMYCIN preparations (lincomycin) in protecting animals infected with Streptococcus viridans,β-hemolytic Streptococcus, Staphylococcus aureus, Diplococcus pneumoniae and Leptospira pomona. It was ineffective in Klebsiella, Pasteurella, Pseudomonas, Salmonella and Shigella infections.

CLINICAL STUDIES

Experience with 345 obstetrical patients receiving this drug revealed no ill effects related to pregnancy. (See PRECAUTIONS, Pregnancy)

PHYSICAL COMPATIBILITIES

Physically compatible for 24 hours at room temperature unless otherwise indicated.

Infusion Solutions
5% Dextrose Injection
10% Dextrose Injection
5% Dextrose and 0.9% Sodium Chloride Injection
10% Dextrose and 0.9% Sodium Chloride Injection
Ringer's Injection

1/6 M Sodium Lactate Injection

Travert® 10%-Electrolyte No. 1
Dextran in Saline 6% w/v

Vitamins in Infusion Solutions
B-Complex
B-Complex with Ascorbic Acid

Antibacterial in Infusion Solutions
Penicillin G Sodium (Satisfactory for 4 hours)
Cephalothin
Tetracycline HCl
Cephaloridine
Colistimethate (Satisfactory for 4 hours)
Ampicillin
Methicillin
Chloramphenicol
Polymyxin B Sulfate

Physically Incompatible with:
Novobiocin
Kanamycin

IT SHOULD BE EMPHASIZED THAT THE COMPATIBLE AND INCOMPATIBLE DETERMINATIONS ARE PHYSICAL OBSERVATIONS ONLY, NOT CHEMICAL DETERMINATIONS. ADEQUATE CLINICAL EVALUATION OF THE SAFETY AND EFFICACY OF THESE COMBINATIONS HAS NOT BEEN PERFORMED.

RX ONLY

Manufactured in Germany

Manufactured for:

X-GEN Pharmaceuticals DJB, Inc.

Big Flats, NY 14814

04/2022

LC-PI-14